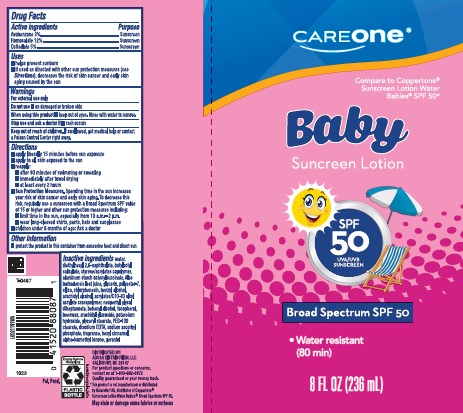 DRUG LABEL: Sunscreen for Babies SPF 50
NDC: 72476-947 | Form: LOTION
Manufacturer: Retail Business Services, LLC
Category: otc | Type: HUMAN OTC DRUG LABEL
Date: 20260206

ACTIVE INGREDIENTS: AVOBENZONE 30 mg/1 mL; HOMOSALATE 120 mg/1 mL; OCTISALATE 50 mg/1 mL
INACTIVE INGREDIENTS: WATER; DIETHYLHEXYL 2,6-NAPHTHALATE; BUTYLOCTYL SALICYLATE; STYRENE/ACRYLAMIDE COPOLYMER (500000 MW); ALUMINUM STARCH OCTENYLSUCCINATE; ALOE VERA LEAF; GLYCERIN; POLYESTER-7; SILICON DIOXIDE; CHLORPHENESIN; BENZYL ALCOHOL; ARACHIDYL ALCOHOL; CARBOMER COPOLYMER TYPE B (ALLYL PENTAERYTHRITOL CROSSLINKED); NEOPENTYL GLYCOL DIHEPTANOATE; DOCOSANOL; TOCOPHEROL; YELLOW WAX; ARACHIDYL GLUCOSIDE; POTASSIUM HYDROXIDE; GLYCERYL MONOSTEARATE; PEG-100 STEARATE; EDETATE DISODIUM ANHYDROUS; SODIUM ASCORBYL PHOSPHATE; .ALPHA.-HEXYLCINNAMALDEHYDE; ISOMETHYL-.ALPHA.-IONONE; GERANIOL

Care One D47AA/D47.001
Sunscreen Lotion for Babies SPF 50

Active ingredients

Avobenzone 3%

Homosalate 12%

Octisalate 5%

Purpose

Sunscreen

Uses

- helps prevent sunburn
- if used as directed with other sun protection measures (See Directions), decreases the risk of skin cancer and early skin aging caused by the sun

Warnings

For external use only

Do not use

- on damaged or broken skin

When using this product

- keep out of eyes. Rinse with water to remove.

Stop use and ask a doctor if

- rash occurs

Keep out of reach of children.

If swallowed, get medical help or contact a Poison Control Center right away.

Directions

- apply liberaly 15 minutes before sun exposure
- apply to all skin exposed to the sun
- reapply:
- after 80 minutes of swimming or sweating
- immediately after towel drying
- at least every 2 hours
- Sun Protection Measures. Spending time in the sun increases your risk of skin cancer and early skin aging. To decrease this rist, regularly use a sunscreen with Broad Spectrum SPF value of 15 or higher and other sun protection measures including:
- limit time in the sun, especialy from 10 a.m. -2 p.m.
- wear long-sleeved shirts, pants, hats and sunglasses
- children under 6 months of age: Ask a doctor

Other information

- protect the product in this container from excessive heat and direct sun

inactive ingredients

water, diethylhexyl 2,6-naphthalate, butyloctyl salicylate, styrene/acrylates copolymer, aluminum starch octenylsuccinate, Aloe barbadensis leaf juice, glycerin, polyester-7, silica, chlorphenesin, benzyl alcohol, arachidyl alcohol, acrylates/C10-30 alkyl acrylate crosspolymer, neopentyl glycol diheptanoate, behenyl alcohol, tocopherol, beeswax, arachidyl glucoside, potassium hydroxide, glyceryl stearate, PEG-100 stearate, disodium EDTA, sodium ascorbyl phosphate, fragrance, hexyl cinnamal, alpha-isomethyl ionone, geraniol

Adverse Reaction

DISTRIBUTED BY ADUSA DISTRIBUTION, LLC

SALISBURY, NC 28147

For product questions or concerns, contact us at 1-833-992-3872

Quality guaranteed or your money back.

Empty Before Recycling

PLASTIC BOTTLE

how2recycle.info

Disclaimers

*This product is not manufactured or distributed by Beiersdorf AG, distributor of Coppertone® Sunscreen Lotion Water BabiesBroad Spectrum SPF 50.

May stain or damage some fabrics or surfaces

Principal Panel Display

CAREone®

Compare to Coppertone® Sunscreen Lotion Water Babies® SPF 50*

Baby Sunscreen Lotion

SPF 50

UVA/UVB SUNSCREEN

Broad Spectrum SPF 50

- Water resistant (80 min)

8 FL OZ (236 mL)